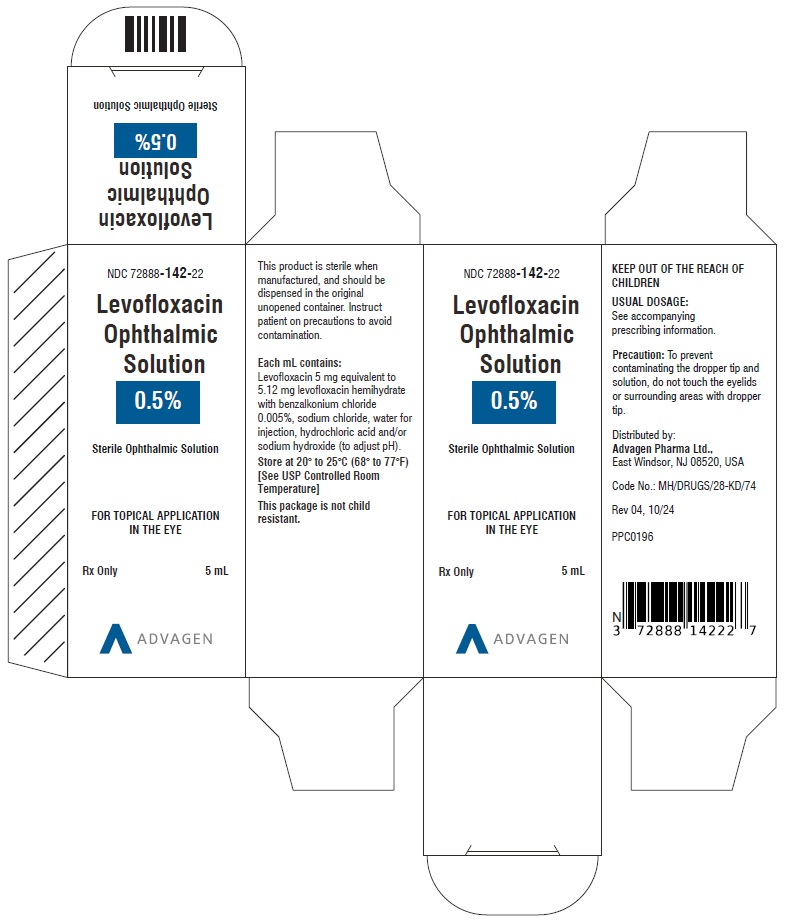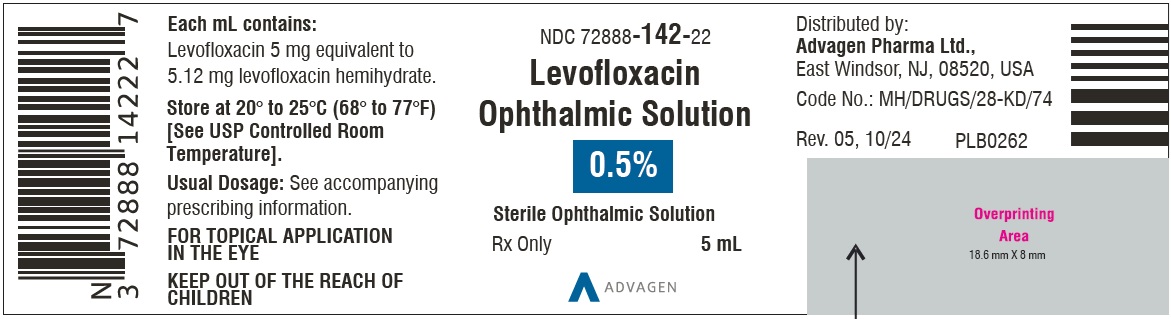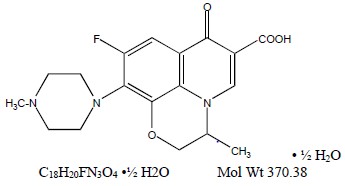 DRUG LABEL: LEVOFLOXACIN
NDC: 72888-142 | Form: SOLUTION
Manufacturer: Advagen Pharma Limited
Category: prescription | Type: HUMAN PRESCRIPTION DRUG LABEL
Date: 20250310

ACTIVE INGREDIENTS: LEVOFLOXACIN 5 mg/1 mL
INACTIVE INGREDIENTS: BENZALKONIUM CHLORIDE; SODIUM CHLORIDE; WATER; HYDROCHLORIC ACID; SODIUM HYDROXIDE

HIGHLIGHTS OF PRESCRIBING INFORMATION

These highlights do not include all the information needed to use LEVOFLOXACIN OPHTHALMIC SOLUTION safely and effectively. See full prescribing information for LEVOFLOXACIN OPHTHALMIC SOLUTION.
LEVOFLOXACIN ophthalmic solution 0.5%
Sterile topical ophthalmic solution
Initial U.S. Approval: 1996

1 INDICATIONS AND USAGE

Levofloxacin ophthalmic solution is indicated for the treatment of bacterial conjunctivitis caused by susceptible strains of the following organisms:

Gram-positive bacteria:

Corynebacterium species*

Staphylococcus aureus

Staphylococcus epidermidis

Streptococcus pneumonia

Streptococcus(Groups C/F)

Streptococcus(Group G)

Viridans group streptococci*

Gram-negative bacteria:

Acinetobacter lwoffii *

Haemophilus influenzae

Serratia marcescens*

*Efficacy for this organism was studied in fewer than 10 infections (1)

2 DOSAGE AND ADMINISTRATION

Days 1 and 2:

Instill one to two drops in the affected eye(s) every 2 hours while awake, up to 8 times per day.

Days 3 through 7:

Instill one to two drops in the affected eye(s) every 4 hours while awake, up to 4 times per day. (2)

3 DOSAGE FORMS AND STRENGTHS

5 mL white LDPE bottle filled with 5 mL sterile ophthalmic solution of levofloxacin, 0.5% (3)

4 CONTRAINDICATIONS

Levofloxacin ophthalmic solution is contraindicated in patients with a history of hypersensitivity to levofloxacin, to other quinolones, or to any of the components in this medication. (4)

5 WARNINGS AND PRECAUTIONS

- Hypersensitivity and anaphylaxis have been reported with systemic use of levofloxacin as well as topical use of other fluoroquinolones, including levofloxacin ophthalmic solution. (5.1)
- Prolonged use may result in the overgrowth of non- susceptible organisms, including fungi. (5.2)
- Patients should not wear contact lenses if they have signs or symptoms of bacterial conjunctivitis. (5.3)

6 ADVERSE REACTIONS

The most frequently reported adverse reactions in the overall study population were transient decreased vision, fever, foreign body sensation, headache, transient ocular burning, ocular pain or discomfort, pharyngitis and photophobia. These reactions occurred in approximately 1 to 3% of patients. Other reported reactions occurring in less than 1% of patients included allergic reactions, lid edema, ocular dryness, and ocular itching. (6)

To report SUSPECTED ADVERSE REACTIONS, contact Advagen Pharma Ltd, at 866-488-0312 or FDA at 1-800-FDA-1088 or www.fda.gov/medwatch

FULL PRESCRIBING INFORMATION

1 INDICATIONS AND USAGE

Levofloxacin ophthalmic solution is indicated for the treatment of bacterial conjunctivitis caused by susceptible strains of the following organisms:

Gram-positive bacteria

Corynebacterium species*

Staphylococcus aureus

Staphylococcus epidermidis

Streptococcus pneumonia

Streptococcus(Groups C/F)

Streptococcus(Group G)

Viridans group streptococci*

Gram-negative bacteria

Acinetobacter lwoffii *

Haemophilus influenzae

Serratia marcescens*

*Efficacy for this organism was studied in fewer than 10 infections

2 DOSAGE AND ADMINISTRATION

Days 1 and 2

Instill one to two drops in the affected eye(s) every 2 hours while awake, up to 8 times per day.

Days 3 through 7

Instill one to two drops in the affected eye(s) every 4 hours while awake, up to 4 times per day.

3 DOSAGE FORMS AND STRENGTHS

5 mL white LDPE bottle filled with 5 mL sterile ophthalmic solution of levofloxacin, 0.5%.

4 CONTRAINDICATIONS

Levofloxacin ophthalmic solution is contraindicated in patients with a history of hypersensitivity to levofloxacin, to other quinolones, or to any of the components in this medication.

5 WARNINGS AND PRECAUTIONS

5.1 Hypersensitivity Reactions

In patients receiving systemically administered quinolones, including levofloxacin, serious and occasionally fatal hypersensitivity (anaphylactic) reactions have been reported, some following the first dose. Some reactions were accompanied by cardiovascular collapse, loss of consciousness, angioedema, (including laryngeal, pharyngeal or facial edema), airway obstruction, dyspnea, urticaria and itching. If allergic reaction to levofloxacin occurs, discontinue the drug. Serious acute hypersensitivity reactions may require immediate emergency treatment. Oxygen and airway management should be administered as clinically indicated.

5.2 Growth of Resistant Organisms with Prolonged Use

As with other anti-infectives, prolonged use may result in overgrowth of non-susceptible organisms, including fungi. If superinfection occurs, discontinue use and institute alternative therapy. Whenever clinical judgment dictates, the patient should be examined with the aid of magnification, such as slit-lamp biomicroscopy, and where appropriate, fluorescein staining.

5.3 Avoidance of Contact Lens Wear

Patients should be advised not to wear contact lenses if they have signs and symptoms of bacterial conjunctivitis.

6 ADVERSE REACTIONS

The most frequently reported adverse reactions in the overall study population were transient decreased vision, fever, foreign body sensation, headache, transient ocular burning, ocular pain or discomfort, pharyngitis and photophobia. These reactions occurred in approximately 1-3% of patients. Other reported reactions occurring in less than 1% of patients included allergic reactions, lid edema, ocular dryness, and ocular itching.

8 USE IN SPECIFIC POPULATIONS

8.1 Pregnancy

Teratogenic Effects

Levofloxacin at oral doses of 810 mg/kg/day in rats caused decreased fetal body weight and increased fetal mortality. No teratogenic effect was observed when rabbits were dosed orally as high as 50 mg/kg/day, at which systemic exposure was approximately 2,250 times that observed at the maximum recommended human ophthalmic dose, or when dosed intravenously as high as 25 mg/kg/day, at which systemic exposure was approximately 1000 times that observed at the maximum recommended human ophthalmic dose.

There are, however, no adequate and well-controlled studies in pregnant women. Levofloxacin should be used during pregnancy only if the potential benefit justifies the potential risk to the fetus.

8.3 Nursing Mothers

Levofloxacin has not been measured in human milk. Based upon data from ofloxacin, it can be presumed that levofloxacin is excreted in human milk. Caution should be exercised when levofloxacin ophthalmic solution is administered to a nursing mother.

8.4 Pediatric Use

Safety and effectiveness in children below the age of six years have not been established. Oral administration of systemic quinolones has been shown to cause arthropathy in immature animals. There is no evidence that the ophthalmic administration of levofloxacin has any effect on weight bearing joints.

8.5 Geriatric Use

No overall differences in safety or effectiveness have been observed between elderly and other adult patients.

11 DESCRIPTION

Levofloxacin Ophthalmic Solution, 0.5% is a sterile topical ophthalmic solution. Levofloxacin is a fluoroquinolone antibacterial active against a broad spectrum of Gram-positive and Gram-negative ocular pathogens. Levofloxacin is a fluorinated 4-quinolone containing a six-member (pyridobenzoxazine) ring from positions 1 to 8 of the basic ring structure. Levofloxacin is the pure (-)-(S)-enantiomer of the racemic drug substance, ofloxacin. It is more soluble in water at neutral pH than ofloxacin.

Chemical Name: (-)-(S)-9-fluoro-2,3-dihydro-3-methyl-10-(4-methyl-1-piperazinyl)-7-oxo-7H-pyrido [1,2,3-de]-1,4 benzoxazine-6-carboxylic acid hemihydrate.

Levofloxacin (hemihydrate) is a light yellow powder.

Each mL of levofloxacin ophthalmic solution, 0.5% contains 5.12 mg of levofloxacin hemihydrate equivalent to 5 mg levofloxacin.

Contains
Levofloxacin 5 mg equivalent to 5.12 mg levofloxacin hemihydrate with benzalkonium chloride 0.005%, sodium chloride, water for injection, hydrochloric acid and/or sodium hydroxide (to adjust pH).

Levofloxacin ophthalmic solution, 0.5% is isotonic and formulated at pH 6.0-6.8 with an osmolality between 285-315 mOsm/kg.

12 CLINICAL PHARMACOLOGY

12.1 Mechanism of Action

Levofloxacin is a member of the fluoroquinolone class of anti-infective drugs. (See 12.4 Microbiology)

12.2 Pharmacokinetics

Levofloxacin concentration in plasma was measured in 15 healthy adult volunteers at various time points during a 15-day course of treatment with levofloxacin ophthalmic solution. The mean levofloxacin concentration in plasma 1 hour postdose, ranged from 0.86 ng/mL on Day 1 to 2.05 ng/mL on Day 15. The highest maximum mean levofloxacin concentration of 2.25 ng/mL was measured on Day 4 following 2 days of dosing every 2 hours for a total of 8 doses per day. Maximum mean levofloxacin concentrations increased from 0.94 ng/mL on Day 1 to 2.15 ng/mL on Day 15, which is more than 1,000 times lower than those reported after standard oral doses of levofloxacin.

Levofloxacin concentration in tears was measured in 30 healthy adult volunteers at various time points following instillation of a single drop of levofloxacin ophthalmic solution. Mean levofloxacin concentrations in tears ranged from 34.9 to 221.1 mcg/mL during the 60-minute period following the single dose. The mean tear concentrations measured 4 and 6 hours postdose were 17.0 and 6.6 mcg/mL. The clinical significance of these concentrations is unknown.

12.3 Microbiology

Levofloxacin is the L-isomer of the racemate, ofloxacin, a quinolone antimicrobial agent. The antibacterial activity of ofloxacin resides primarily in the L-isomer. The mechanism of action of levofloxacin and other fluoroquinolone antimicrobials involves the inhibition of bacterial topoisomerase IV and DNA gyrase (both of which are type II topoisomerases), enzymes required for DNA replication, transcription, repair, and recombination.

Levofloxacin has in vitroactivity against a wide range of Gram-negative and Gram-positive microorganisms and is often bactericidal at concentrations equal to or slightly greater than inhibitory concentrations.

Fluoroquinolones, including levofloxacin, differ in chemical structure and mode of action from β- lactam antibiotics and aminoglycosides, and therefore may be active against bacteria resistant to β- lactam antibiotics and aminoglycosides. Additionally, β-lactam antibiotics and aminoglycosides may be active against bacteria resistant to levofloxacin.

Resistance to levofloxacin due to spontaneous mutation in vitrois a rare occurrence (range: 10^-9to 10^-10)

Levofloxacin has been shown to be active against most strains of the following microorganisms, both in vitroand in clinical infections as described in the INDICATIONS AND USAGE section:

Aerobic gram-positive microorganisms

Corynebacterium species*

Staphylococcus aureus

Staphylococcus epidermidis

Streptococcus pneumonia

Streptococcus(Groups C/F)

Streptococcus(Group G)

Viridans group streptococci*

Aerobic gram-negative microorganisms

Acinetobacter lwoffii*

Haemophilus influenzae

Serratia marcescens*

*Efficacy for this organism was studied in fewer than 10 infections.

The following in vitrodata are also available, but their clinical significance in ophthalmic infections is unknown. The safety and effectiveness of levofloxacin in treating ophthalmological infections due to these microorganisms have not been established in adequate and well- controlled trials.

These organisms are considered susceptible when evaluated using systemic breakpoints. However, a correlation between the in vitrosystemic breakpoint and ophthalmological efficacy has not been established. The list of organisms is provided as guidance only in assessing the potential treatment of conjunctival infections. Levofloxacin exhibits in vitrominimal inhibitory concentrations (MICs) of 2 mcg/mL or less (systemic susceptible breakpoint) against most (≥90%) strains of the following ocular pathogens:

Aerobicgram-positive microorganisms

Enterococcus faecalis

Staphylococcus saprophyticus

Streptococcus agalactiae

Streptococcus pyogenes

Aerobic gram-negative microorganisms

Acinetobacter anitratus

Acinetobacter baumannii

Citrobacter koseri

Citrobacter freundii

Enterobacter aerogenes

Enterobacter agglomerans

Enterobacter cloacae

Escherichia coli

Haemophilus parainfluenzae

Klebsiella oxytoca

Klebsiella pneumonia

Legionella pneumophila

Moraxella catarrhalis

Morganella morganii

Neisseria gonorrhoeae

Proteus mirabilis

Proteus vulgaris

Providencia rettgeri

Providencia stuartii

Pseudomonas aeruginosa

Pseudomonas fluorescens

13 NONCLINICAL TOXICOLOGY

13.1 Carcinogenesis, Mutagenesis, Impairment of Fertility

In a long term carcinogenicity study in rats, levofloxacin exhibited no carcinogenic or tumorigenic potential following daily dietary administration for 2 years at doses up to 100 mg/kg/day, corresponding to plasma levels that were 1235 times the maximum clinical exposure, based on Cmax.

Levofloxacin was not mutagenic in the following assays: Ames bacterial mutation assay (S. typhimuriumand E. coli), CHO/HGPRT forward mutation assay, mouse micronucleus test, mouse dominant lethal test, rat unscheduled DNA synthesis assay, and the in vivomouse sister chromatid exchange assay. It was positive in the in vitrochromosomal aberration (CHL cell line) and in vitrosister chromatid exchange (CHL/IU cell line) assays. Levofloxacin caused no impairment of fertility or reproduction in rats at oral doses as high as 360 mg/kg/day, at which systemic exposure was estimated to be 23,000 times that at the maximum recommended human ophthalmic dose.

14 CLINICAL STUDIES

In randomized, double-masked, multicenter controlled clinical trials where patients were dosed for 5 days, Levofloxacin ophthalmic® demonstrated clinical cures in 79% of patients treated for bacterial conjunctivitis on the final study visit day (day 6 to10). Microbial outcomes for the same clinical trials demonstrated an eradication rate for presumed pathogens of 90%.

16 HOW SUPPLIED/STORAGE HANDLING

Levofloxacin Ophthalmic Solution, 0.5% is a clear light yellow solution supplied in a white LDPE bottle with translucent LDPE nozzle and tan coloured HDPE cap in the following size:

5 mL filled in 5 mL bottle – NDC 72888-142-22

Storage:

Store at 20º to 25°C (68º to 77°F) [See USP Controlled Room Temperature].

17 PATIENT COUNSELING INFORMATION

17.1 Avoid Contamination of the Product

Advise patients to avoid contaminating the applicator tip with material from the eye, finger, or other source.

17.2 Avoid Contact Lens Wear

Advise patients not to wear contact lenses if they have signs and symptoms of bacterial conjunctivitis.

17.3 Hypersensitivity Reactions

Systemically administered quinolones, including levofloxacin, have been associated with hypersensitivity reactions, even following a single dose. Advise patients to discontinue use immediately and contact their physician at the first sign of a rash or allergic reaction.

Distributed by:

Advagen Pharma Ltd.,

East Windsor, NJ 08520, USA

Rev. 02/2025

PACKAGE LABEL.PRINCIPAL DISPLAY PANEL

Levofloxacin Ophthalmic Solution, 0.5% Sterile Ophthalmic Solution - NDC 72888-142-22 - 5 mL Carton Label

Levofloxacin Ophthalmic Solution, 0.5% Sterile Ophthalmic Solution - NDC 72888-142-22 - 5 mL Container Label